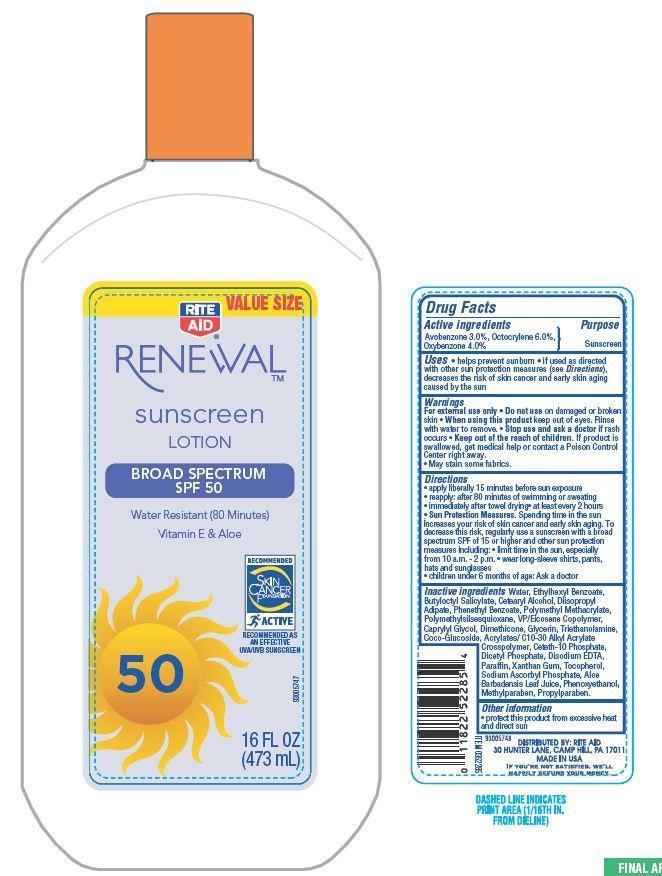 DRUG LABEL: Rite Aid RENEWAL
NDC: 11822-9026 | Form: LOTION
Manufacturer: RITE AID CORPORATION
Category: otc | Type: HUMAN OTC DRUG LABEL
Date: 20130722

ACTIVE INGREDIENTS: AVOBENZONE 3 g/100 g; OXYBENZONE 6 g/100 g; OCTOCRYLENE 4 g/100 g
INACTIVE INGREDIENTS: WATER; 2-ETHYLHEXYL BENZOATE; PROPYLENE GLYCOL; CETOSTEARYL ALCOHOL; BUTYLOCTYL SALICYLATE; DIISOPROPYL ADIPATE; NEOPENTYL GLYCOL DIHEPTANOATE; PHENETHYL BENZOATE; CAPRYLYL GLYCOL; DIMETHICONE; GLYCERIN; TROLAMINE; COCO GLUCOSIDE; CETETH-10 PHOSPHATE; DIHEXADECYL PHOSPHATE; EDETATE DISODIUM; PARAFFIN; TOCOPHEROL; SODIUM ASCORBYL PHOSPHATE ; ALOE VERA LEAF; PHENOXYETHANOL; METHYLPARABEN; PROPYLPARABEN; XANTHAN GUM

Drug Facts

Active Ingredients

Avobenzone 3.0 %

Octocrylene 6.0%

Oxybenzone 4.0%

Purpose

Sunscreen

Uses

- helps prevent sunburn
- if used as directed with other sun protection measures (see Directions) decrease the risk of skin cancer and early skin aging caused by the sun

Warnings

For External use only

Do not use on damaged or broken skin

When using this product

- keep out of eyes. Rinse with water to remove.

stop use and ask a doctor if

rash occurs.

Keep out of reach of children.

If product is swallowed get medical help or contact a Poison Control Center right away.

- May stain some fabrics.

Other Information

protect this product from excessive heat and direct sun

Directions

- apply liberally 15 minutes before sun exposure
- reapply: after 80 minutes of swimming or sweating
- immediately after towel drying
- at least every 2 hours

Sun protection measures.

Spending time in the sun increase your risk of skin cancer and early skin aging. To decrease this risk regularly use a sunscreen with a broad spectrum SPF of 15 or higher and other sun protection measures including:

- Limit time in the sun, especially from 10 am - 2 pm
- Wear long sleeves shirts, pants, hats and sunglasses
- children under 6 month of age: Ask a doctor

Inactive Ingredients

Water, Ethylhexyl Benzoate, Butyloctyl Salicylate, Cetearyl Alcohol, Diisopropyl Adipate, Phenethyl Benzoate, Polymethyl Methacrylate, Polymethylsilsesquioxane, VP/Eicosene Copolymer, Caprylyl Glycol, Dimethicone, Glycerin, Triethanolamine, Coco-Glucoside, Acrylates/C10-30 Alkyl Acrylate Crosspolymer, Ceteth-10 Phosphate, Dicetyl Phosphate, Disodium EDTA, Paraffin, Xanthan Gum, Tocopherol, Sodium Ascorbyl Phosphate, Aloe Barbadensis Leaf Juice, Phenoxyethanol, Methylparaben, Propylparaben.

Principal Display Panel

VALUE SIZE

RITE

AID

RENEWAL

sunscreen

LOTION

BROAD SPECTRUM

SPF 50

Water Resistant (80 Minutes)

Vitamin E and Aloe

RECOMMENDED

SKIN

CANCER

FOUNDATION

ACTIVE

RECOMMENDED AS

AN EFFECTIVE

UVA.UVB SUNSCREEN

16 FL OZ

(473 mL)